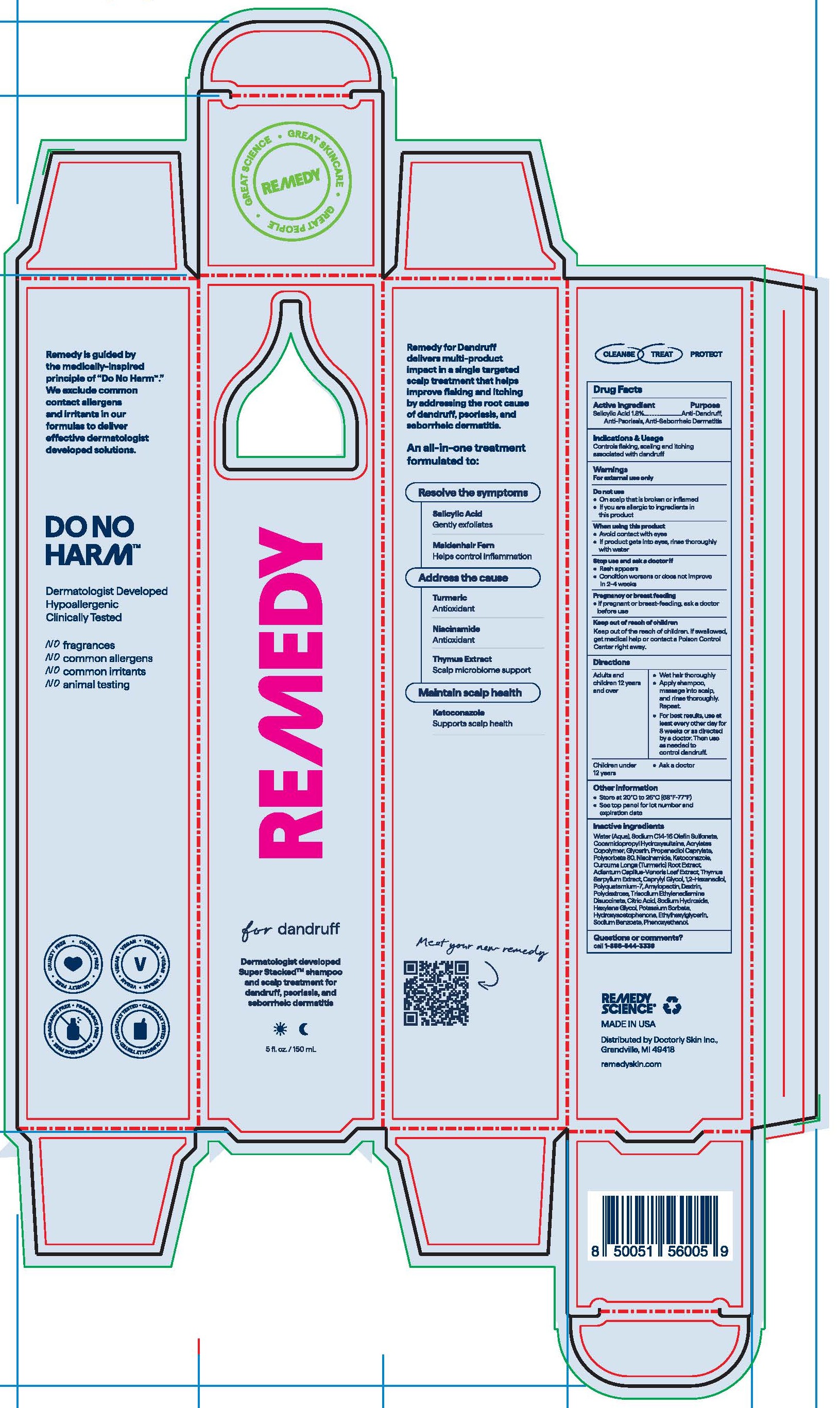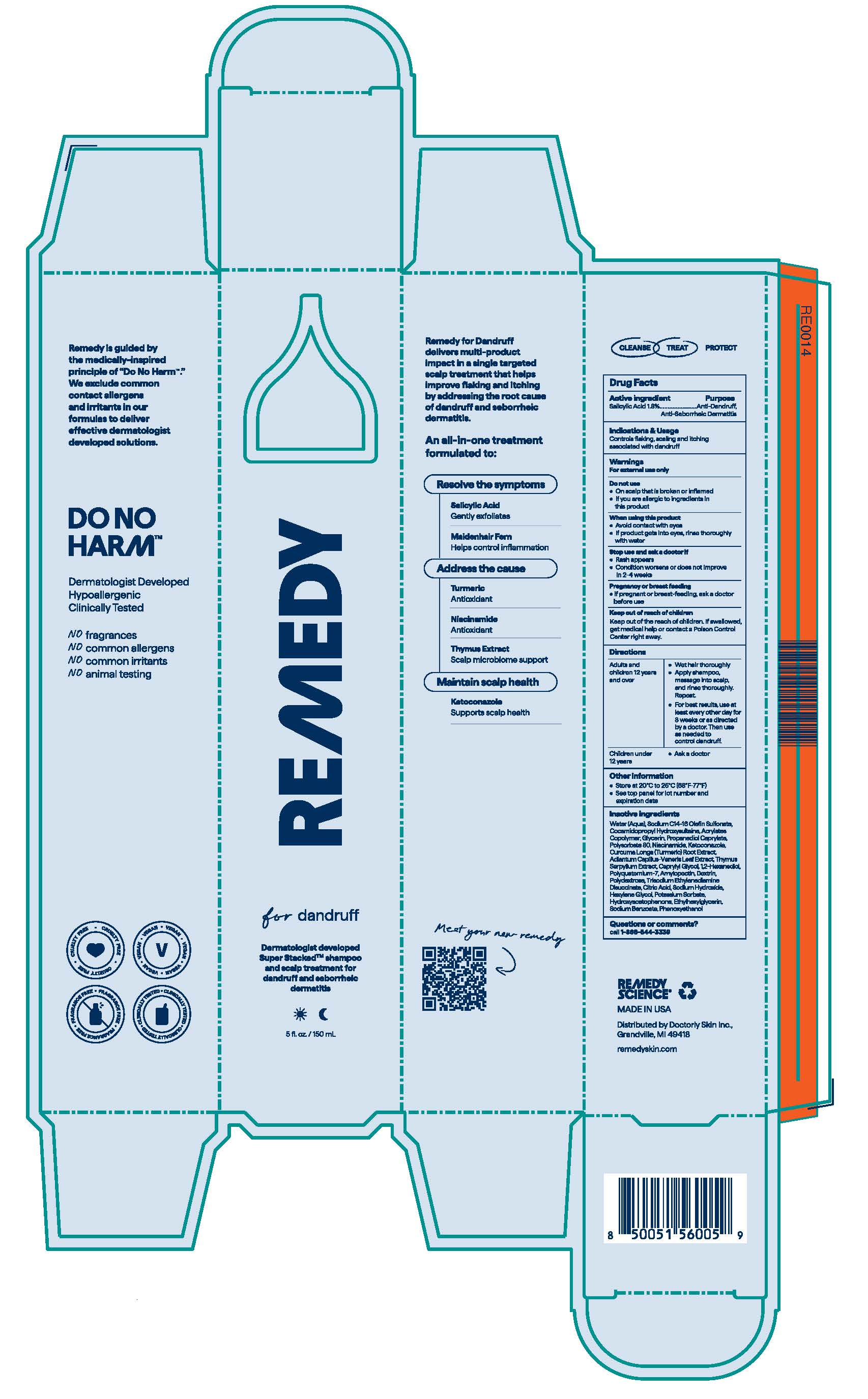 DRUG LABEL: Remedy for Dandruff
NDC: 85153-001 | Form: SHAMPOO
Manufacturer: Doctorly Skin Inc.
Category: otc | Type: HUMAN OTC DRUG LABEL
Date: 20251210

ACTIVE INGREDIENTS: SALICYLIC ACID 18 mg/1 mL
INACTIVE INGREDIENTS: POTASSIUM SORBATE; GLYCERIN; DEXTRIN, POTATO; 1,2-HEXANEDIOL; ETHYLHEXYLGLYCERIN; HYDROXYACETOPHENONE; THYMUS SERPYLLUM; TURMERIC; AMYLOPECTIN, UNSPECIFIED SOURCE; PROPANEDIOL CAPRYLATE; SODIUM C14-16 OLEFIN SULFONATE; KETOCONAZOLE; ADIANTUM CAPILLUS-VENERIS LEAF; WATER; SODIUM BENZOATE; CAPRYLYL GLYCOL; POLYDEXTROSE; POLYSORBATE 80; COCAMIDOPROPYL HYDROXYSULTAINE; LUVISET 360; NIACINAMIDE; SODIUM HYDROXIDE; POLYQUATERNIUM-7; TRISODIUM ETHYLENEDIAMINE DISUCCINATE; HEXYLENE GLYCOL; CITRIC ACID MONOHYDRATE; PHENOXYETHANOL

Active Ingredient

Salicylic Acid 1.8%

Purpose

Anti-Dandruff, Anti-Psoriasis, Anti-Seborrheic Dermatitis

Indications & Usage

Controls flaking, scaling and itching associated with dandruff.

Warnings

For external use only

Do not use

o On scalp that is broken or inflamed

o If you are allergic to ingredients in this product

When using this product

- Avoid contact with eyes
- If product gets into eyes, rinse thoroughly with water

Stop use and ask a doctor if

- Rash appears
- Condition worsens or does not improve in 2-4 weeks

Pregnancy or breast feeding

- If pregnant or breast-feeding, ask a doctor before use

Keep out of reach of children. If swallowed, get medical help or contact a Poison Control Center right away

Directions

Adults and children 12 years ad over | - Wet hair thoroughly - Apply shampoo, masage into scalp, and rinse thoroughly. Repeat - For best results, use at least every other day for 8 weeks or as directed by a doctor. Then use as needed to control dandruff.
Children under 12 years | - Ask a doctor

Other information

- Store at 20°C to 25°C (68°F-77°F)
- See top panel for lot number and expiration date

Inactive ingredients

Water (Aqua), Sodium C14-16 Olefin Sulfonate, Cocamidopropyl
Hydroxysultaine, Acrylates Copolymer, Glycerin, Propanediol
Caprylate, Polysorbate 80, Niacinamide, Ketoconazole, Curcuma
Longa (Turmeric) Root Extract, Adiantum Capillus-Veneris Leaf
Extract, Thymus Serpyllum Extract, Caprylyl Glycol, 1,2-Hexanediol,
Polyquaternium-7, Amylopectin, Dextrin, Polydextrose, Trisodium
Ethylenediamine Disuccinate, Citric Acid, Sodium Hydroxide,
Hexylene Glycol, Potassium Sorbate, Hydroxyacetophenone,
Ethylhexylglycerin, Sodium Benzoate, Phenoxyethanol

Questions or comments?

Call 1-866-544-3339